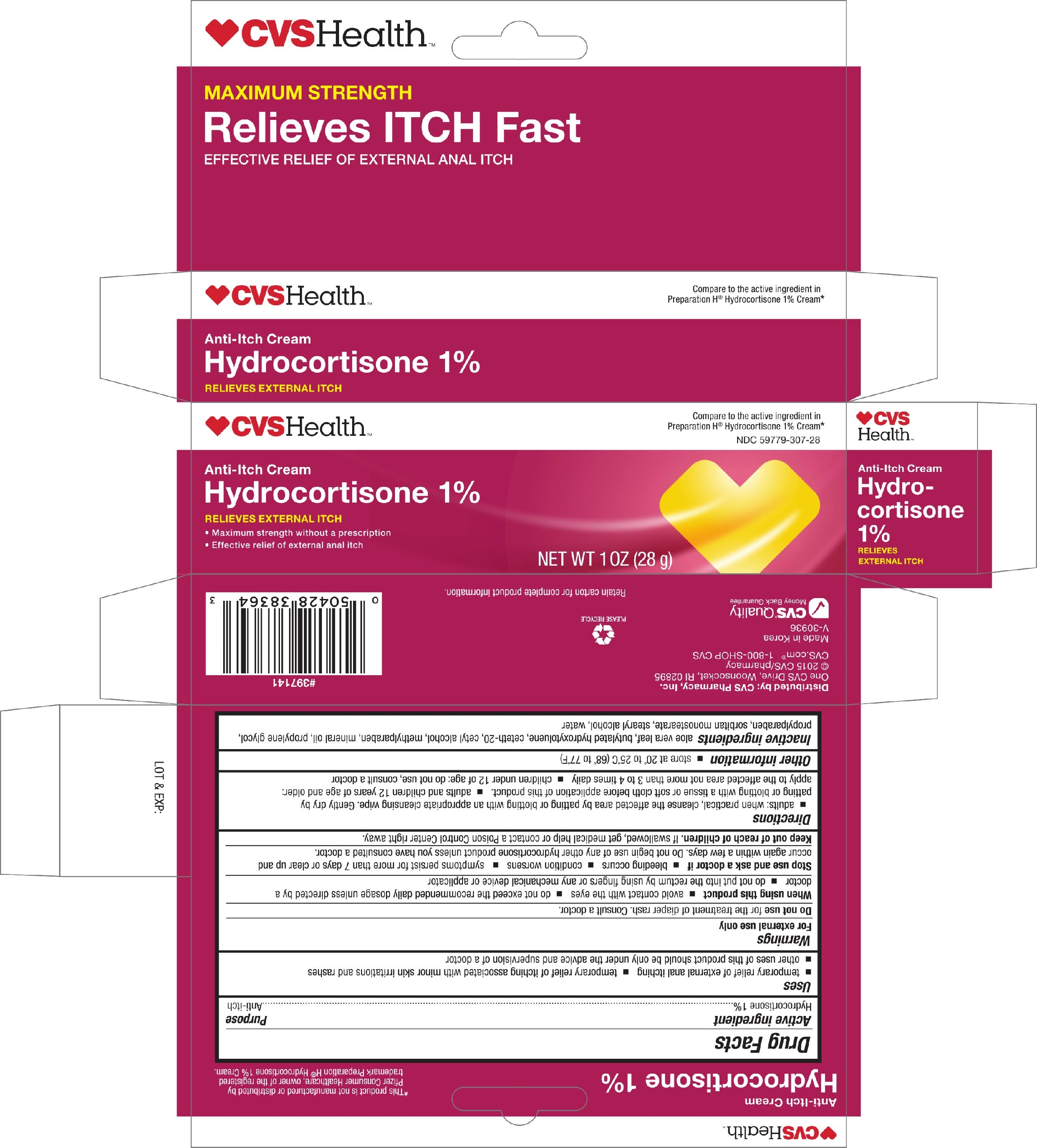 DRUG LABEL: CVS Pharmacy Anti-itch
NDC: 59779-307 | Form: CREAM
Manufacturer: CVS
Category: otc | Type: HUMAN OTC DRUG LABEL
Date: 20180105

ACTIVE INGREDIENTS: HYDROCORTISONE 1 g/100 g
INACTIVE INGREDIENTS: ALOE VERA LEAF; BUTYLATED HYDROXYTOLUENE; CETETH-20; CETYL ALCOHOL; METHYLPARABEN; MINERAL OIL; PROPYLENE GLYCOL; PROPYLPARABEN; SORBITAN MONOSTEARATE; STEARYL ALCOHOL; WATER

CVS Anti-Itch Cream Hydrocortisone 1% 1oz 30208

Active ingredient Purpose

Hydrocortisone 1%.............................................................Anti-itch

Uses

- temporary relief of external anal itching
- temporary relief of itching associated with minor skin irritations and rashes
- other uses of this product should be only under the advice and supervision of a doctor

Warnings

For external use only

Do not use for the treatment of diaper rash. Consult a doctor.

When using this product

- avoid contact with the eyes
- do not exceed the recommended daily dosage unless directed by a doctor
- do not put into the rectum by using fingers or any mechanical device or applicator

Stop use and ask a doctor if

- bleeding occurs
- condition worsens
- symptoms persist for more than 7 days or clear up and occur again within a few days. Do not being use of any other hydrocortisone product unless you have consulted a doctor.

Keep out of reach of children. If swallowed, get medical help or contact a Poison Control Center right away.

Directions

- adults: when practical, cleanse the affected area by patting or blotting with an appropriate cleansing wipe. Gently dry by patting or blotting with a tissue or soft cloth before application of this product.
- adults and children 12 years of age and older: apply to the affected area not more than 3 to 4 times daily
- children under 12 of age: do not use, consult a doctor

Other information

- store at 20° and 25°C (68° to 77°F)

INACTIVE INGREDIENT

Inactive ingredients aloe vera leaf, butylated hydroxytoluene, ceteth-20, cetyl alcohol, methylparaben, mineral oil, propylene glycol, propylparaben, sorbitan monostearate, stearyl alcohol, water

DOSAGE AND ADMINISTRATION

Distributed by: CVS Pharmacy, Inc.

One CVS Drive, Woonsocket, RI 02895

Made in Korea